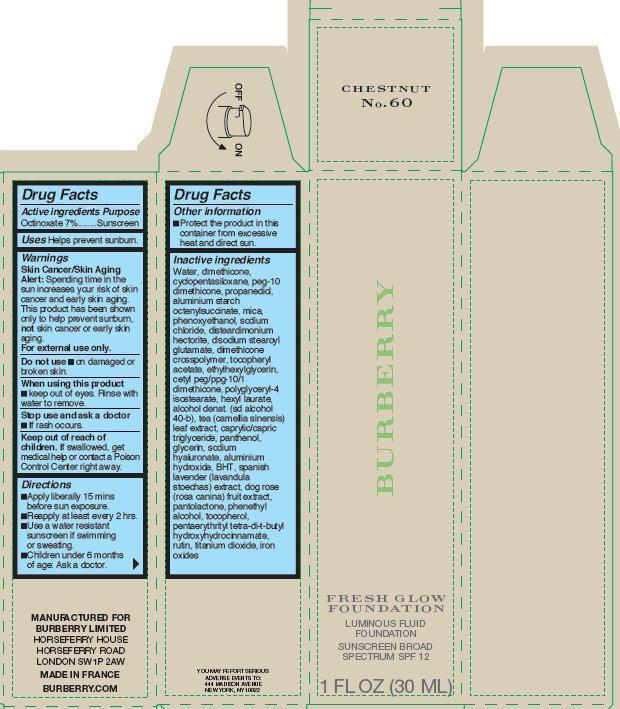 DRUG LABEL: Burberry Fresh Glow Foundation Luminous Fluid Chestnut No. 60
NDC: 69038-007 | Form: CREAM
Manufacturer: Burberry Limited
Category: otc | Type: HUMAN OTC DRUG LABEL
Date: 20190918

ACTIVE INGREDIENTS: OCTINOXATE 70 mg/1 mL
INACTIVE INGREDIENTS: WATER; DIMETHICONE; CYCLOMETHICONE 5; PROPANEDIOL; ALUMINUM STARCH OCTENYLSUCCINATE; MICA; PHENOXYETHANOL; SODIUM CHLORIDE; DISTEARDIMONIUM HECTORITE; DISODIUM STEAROYL GLUTAMATE; .ALPHA.-TOCOPHEROL ACETATE; ETHYLHEXYLGLYCERIN; POLYGLYCERYL-4 ISOSTEARATE; HEXYL LAURATE; TEA LEAF; MEDIUM-CHAIN TRIGLYCERIDES; PANTHENOL; GLYCERIN; HYALURONATE SODIUM; ALUMINUM HYDROXIDE; BUTYLATED HYDROXYTOLUENE; ROSA CANINA FRUIT; PANTOLACTONE, (R)-; PHENYLETHYL ALCOHOL; TOCOPHEROL; PENTAERYTHRITOL TETRAKIS(3-(3,5-DI-TERT-BUTYL-4-HYDROXYPHENYL)PROPIONATE); RUTIN; TITANIUM DIOXIDE; FERRIC OXIDE RED

Burberry Fresh Glow Foundation Luminous Fluid Chestnut No. 60

Active Ingredients

Octinoxate 7%

Purpose

Sunscreen

Uses

Helps prevent sunburn.

Warnings

Skin Cancer/Skin Aging Alert: Spending time in the sun increases your risk of skin cancer and earlyskin aging. This product has been shown only to help prevent sunburn, not skin cancer or early skin aging
For external use only.

Do not use

On damaged or broken skin.

When using this product

- Keep out of eyes. Rinse with water to remove.

Stop use and ask a doctor

- If rash occurs.

Keep out of reach of children.

If swallowed, get medical help or contact a Poison Control Center right away.

Directions

- Apply liberally 15 mins before sun exposure.
- Reapply at least every 2 hrs.
- Use a water resistant sunscreen if swimming or sweating.
- Children under 6 months of age: Ask a doctor.

Other information

- Protect the product in this container from excessive heat and direct sun.

Inactive ingredients

water, dimethicone, cyclopentasiloxane, peg-10 dimethicone, propanediol, aluminium starch octenylsuccinate, mica, phenoxyethanol, sodium chloride, disteardimonium hectorite, disodium stearoyl glutamate, dimethicone crosspolymer, tocopheryl acetate, ethylhexylglycerin, cetyl peg/ppg-10/1 dimethicone, polyglyceryl-4 isostearate, hexyl laurate, alcohol denat. (sd alcohol 40-b), tea (camellia sinensis) leaf extract, caprylic/capric triglyceride, panthenol, glycerin, sodium hyaluronate, aluminium hydroxide, BHT, spanish lavender (lavandula stoechas) extract, dog rose (rosa canina) fruit extract, pantolactone, phenethyl alcohol, tocopherol, pantaerythrityl tetra-di-t-butyl hydroxyhydrocinnamate, rutin, titanium dioxide, iron oxides.

Manufactured for Burberry Limited Horseferry House Horseferry Road London SW1P2AW Made In France Burberry.com
You May Report Serious Adverse Events to: 444 Madison Avenue New York, NY 10022

PACKAGE LABEL

CHESTNUT No.60 BURBERRY FRESH GLOW FOUNDATION LUMINOUS FLUID FOUNDATION SUNSCREEN BROAD SPECTRUM SPF 12 1 FL OZ (30 ML)